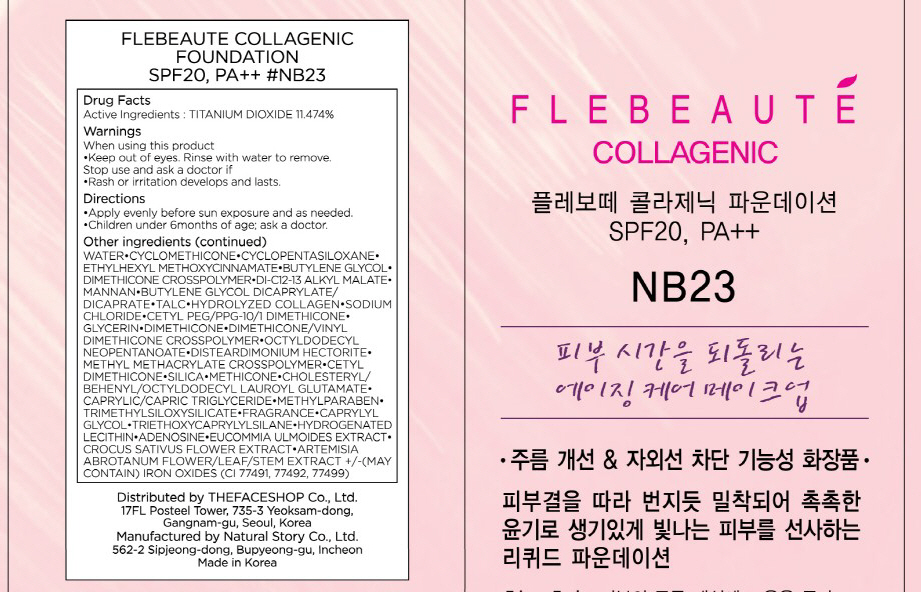 DRUG LABEL: FLEBEAUTE COLLAGENIC FOUNDATION SPF20
NDC: 51523-005 | Form: CREAM
Manufacturer: THEFACESHOP CO., LTD.
Category: otc | Type: HUMAN OTC DRUG LABEL
Date: 20100712

ACTIVE INGREDIENTS: TITANIUM DIOXIDE 4.01 mL/35 mL

Drug Facts

Active Ingredient: TITANIUM DIOXIDE

Inactive Ingredients:
WATER, CYCLOMETHICONE, CYCLOPENTASILOXANE, ETHYLHEXYL METHOXYCINNAMATE, BUTYLENE GLYCOL, DIMETHICONE CROSSPOLYMER, DI-C12-13 ALKYL MALATE,
MANNAN, BUTYLENE GLYCOL DICAPRYLATE/DICAPRATE, TALC, HYDROLYZED COLLAGEN, SODIUM CHLORIDE, CETYL PEG/PPG-10/1 DIMETHICONE, GLYCERIN,
DIMETHICONE, DIMETHICONE/VINYL DIMETHICONE CROSSPOLYMER, OCTYLDODECYL NEOPENTANOATE, DISTEARDIMONIUM HECTORITE, METHYL METHACRYLATE CROSSPOLYMER,
CETYL DIMETHICONE, SILICA, METHICONE, CHOLESTERYL/BEHENYL/OCTYLDODECYL LAUROYL GLUTAMATE, CAPRYLIC/CAPRIC TRIGLYCERIDE, METHYLPARABEN,
TRIMETHYLSILOXYSILICATE, FRAGRANCE, CAPRYLYL GLYCOL, TRIETHOXYCAPRYLYLSILANE, HYDROGENATED LECITHIN, ADENOSINE, EUCOMMIA ULMOIDES EXTRACT,
CROCUS SATIVUS FLOWER EXTRACT, ARTEMISIA ABROTANUM FLOWER/LEAF/STEM EXTRACT
(MAY CONTAIN) IRON OXIDES(CI 77491, 77492, 77499)

Warnings:
When using this product
Keep out of eyes. Rinse with water to remove.
Stop use and ask a doctor if
Rash or irritation develops and lasts.
Directions:
Apply evenly before sun exposure and as needed.
Children under 6months of age; ask a doctor.